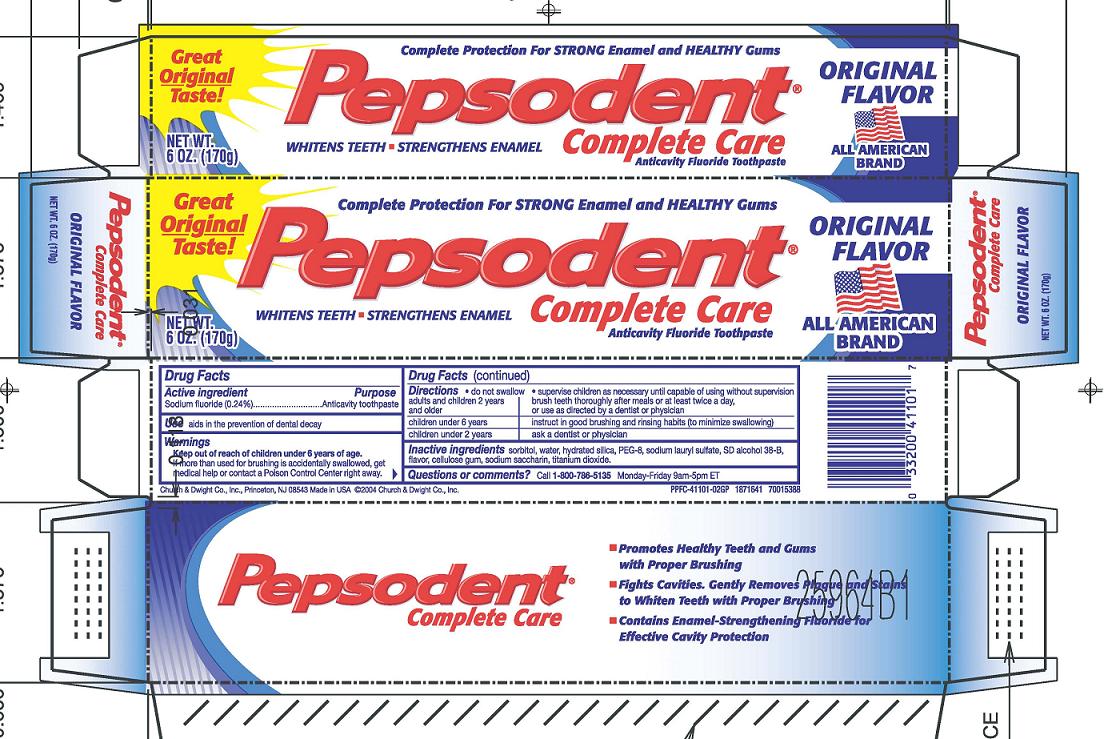 DRUG LABEL: Pepsodent Complete Care
NDC: 10237-651 | Form: PASTE, DENTIFRICE
Manufacturer: Church & Dwight Co., Inc.
Category: otc | Type: HUMAN OTC DRUG LABEL
Date: 20241121

ACTIVE INGREDIENTS: SODIUM FLUORIDE 2.4 mg/1 g
INACTIVE INGREDIENTS: SORBITOL; WATER; HYDRATED SILICA; POLYETHYLENE GLYCOL 400; SODIUM LAURYL SULFATE; ALCOHOL; CARBOXYMETHYLCELLULOSE SODIUM, UNSPECIFIED; SACCHARIN SODIUM; TITANIUM DIOXIDE

Pepsodent Complete Care Original

Active ingredients
Sodium fluoride (0.24%)

Purpose
Anticavity toothpaste

INDICATIONS AND USAGE

Use aids in the prevention of dental decay

Warnings
Keep out of reach of children under 6 years of age .

WARNINGS

If more than used for brushing is accidentally swallowed, get medical help or contact a Poison Control Center right away.

DOSAGE AND ADMINISTRATION

Directions do not swallow supervise children as necessary until capable of using without supervision

adults and children 2 years and older brush teeth thoroughly after meals or at least twice a day, or use as directed by a dentist or physician
children under 6 years instruct in good brushing and rinsing habits (to minimize swallowing)
children under 2 years ask a dentist or physician

INACTIVE INGREDIENT

Inactive ingredients sorbitol, water, hydrated silica, PEG-8, sodium lauryl sulfate, SD alcohol 38-B, flavor, cellulose gum, sodium saccharin, titanium dioxide.

Questions or comments? Call 1-800-786-5135Monday-Friday 9am-5pm ET

Principal Display Panel

Great Original Taste! Complete Protection For STRONGEnamel and HEALTHYGums ORIGINAL FLAVOR

Pepsodent Complete Care

Whitens Teeth Strengthens Enamel

Complete Care Anticavity Fluoride Toothpaste All American Brand

NET WT. 5.5 OZ. (156g)